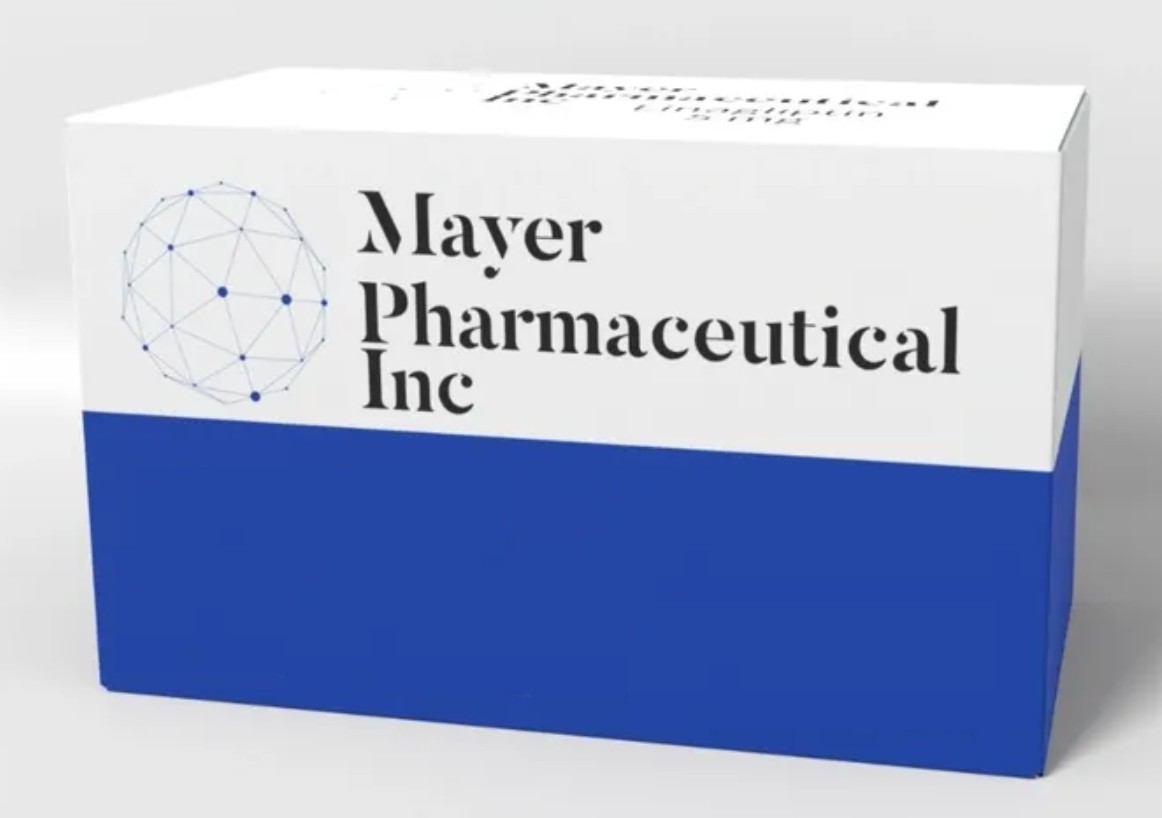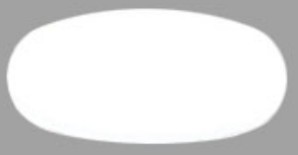 DRUG LABEL: CELECOXIB
NDC: 82922-101 | Form: TABLET
Manufacturer: Truemed Group LLC
Category: prescription | Type: HUMAN PRESCRIPTION DRUG LABEL
Date: 20230414

ACTIVE INGREDIENTS: CELECOXIB 200 mg/1 1

CELECOXIB